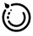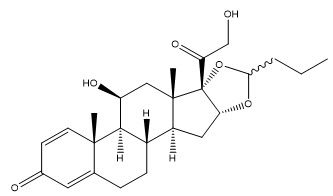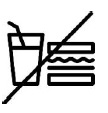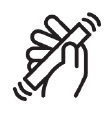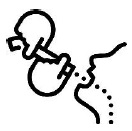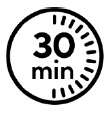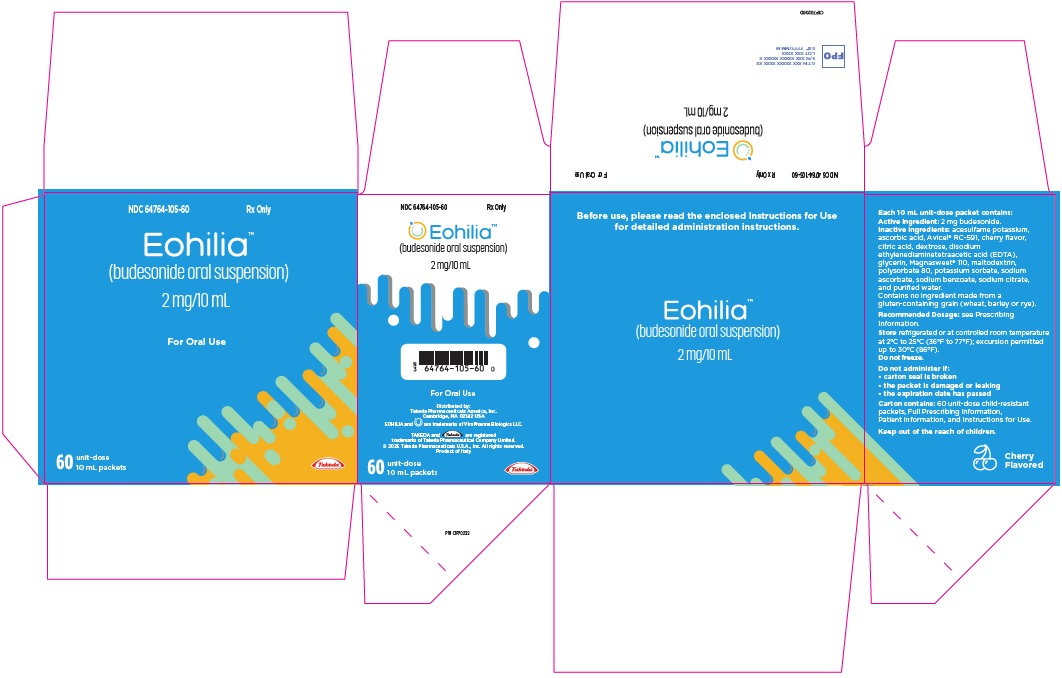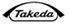 DRUG LABEL: Eohilia
NDC: 64764-105 | Form: SUSPENSION
Manufacturer: TAKEDA PHARMACEUTICALS AMERICA, INC.
Category: prescription | Type: HUMAN PRESCRIPTION DRUG LABEL
Date: 20250203

ACTIVE INGREDIENTS: Budesonide 2 mg/10 mL
INACTIVE INGREDIENTS: MICROCRYSTALLINE CELLULOSE; Maltodextrin; DEXTROSE MONOHYDRATE; EDETATE DISODIUM; ANHYDROUS CITRIC ACID; SODIUM CITRATE, UNSPECIFIED FORM; Polysorbate 80; Glycerin; Sodium Ascorbate; Ascorbic Acid; Sodium Benzoate; Potassium Sorbate; Acesulfame Potassium; WATER; AMMONIUM GLYCYRRHIZATE; CHERRY

HIGHLIGHTS OF PRESCRIBING INFORMATION

These highlights do not include all the information needed to use EOHILIA safely and effectively. See full prescribing information for EOHILIA.
EOHILIA™ (budesonide oral suspension)
Initial U.S. Approval: 1997

1 INDICATIONS AND USAGE

EOHILIA is a corticosteroid indicated for 12 weeks of treatment in adult and pediatric patients 11 years of age and older with eosinophilic esophagitis (EoE). (1)

Limitations of Use

EOHILIA has not been shown to be safe and effective for the treatment of EoE for longer than 12 weeks. (1, 2.1, 14)

2 DOSAGE AND ADMINISTRATION

- Recommended dosage: 2 mg orally twice daily for 12 weeks. (2.1)
- See full prescribing information for preparation and important administration instructions. (2.2)

3 DOSAGE FORMS AND STRENGTHS

Oral suspension: 2 mg/10 mL unit-dose packets. (3)

4 CONTRAINDICATIONS

Hypersensitivity to budesonide. (4)

5 WARNINGS AND PRECAUTIONS

- Hypercorticism and Adrenal Axis Suppression: May occur with treatment; monitor for signs and symptoms and consider reducing the dosage. (5.1, 8.6)
- Immunosuppression and Increased Risk of Infection: Increased risk of viral, bacterial, fungal, protozoan, and helminthic infections, including potentially fatal varicella and measles infection. Monitor patients for new or worsening localized or systemic infection, including oropharyngeal and esophageal candidiasis and consider drug discontinuation. Avoid use in patients with fungal infections, Strongyloides infestation, cerebral malaria, and ocular herpes simplex. Screen for hepatitis B infection. (5.2)
- Erosive Esophagitis: Advise patients or caregivers to report new or worsening signs or symptoms of erosive esophagitis; consider endoscopic evaluation as appropriate. (5.3)
- Effect on Growth: Use of corticosteroids may cause a reduction in growth velocity in pediatric patients; monitor growth during treatment. (5.4)
- Symptoms of Steroid Withdrawal in Patients Transferred from Other Systemic Corticosteroids: Taper slowly from corticosteroids with high systemic effects; monitor for withdrawal symptoms and unmasking of allergies (rhinitis, eczema). (5.5)
- Other Corticosteroid Effects: Monitor patients with concomitant conditions where corticosteroids may have unwanted effects (e.g., hypertension, diabetes mellitus). (5.6)
- Kaposi’s Sarcoma: Reported to occur in patients receiving corticosteroid therapy, most often for chronic conditions. (5.7)

6 ADVERSE REACTIONS

Most common adverse reactions (≥2%) are: respiratory tract infection, gastrointestinal mucosal candidiasis, headache, gastroenteritis, throat irritation, adrenal suppression, and erosive esophagitis. (6.1)

To report SUSPECTED ADVERSE REACTIONS, contact Takeda Pharmaceuticals America, Inc. at 1-877-TAKEDA-7 (1-877-825-3327) or FDA at 1-800-FDA-1088 or www.fda.gov/medwatch.

7 DRUG INTERACTIONS

CYP3A4 Inhibitors (e.g., ketoconazole, grapefruit juice): Can increase systemic budesonide concentrations. Avoid concomitant use. (2.2, 7.1)

8 USE IN SPECIFIC POPULATIONS

- Pregnancy: Based on animal data, may cause fetal harm. (8.1)
- Hepatic Impairment: Use is not recommended in severe hepatic impairment. Monitor patients with moderate hepatic impairment for signs and/or symptoms of hypercorticism. (5.1, 8.6)

FULL PRESCRIBING INFORMATION

1 INDICATIONS AND USAGE

EOHILIA™ is indicated for 12 weeks of treatment in adult and pediatric patients 11 years of age and older with eosinophilic esophagitis (EoE).

Limitations of Use

EOHILIA has not been shown to be safe and effective for the treatment of EoE for longer than 12 weeks [see Dosage and Administration (2.1), Clinical Studies (14)].

2 DOSAGE AND ADMINISTRATION

2.1 Recommended Dosage

- The recommended dosage is 2 mg orally twice daily for 12 weeks.

2.2 Preparation and Important Administration Instructions

- Do NOT take EOHILIA with food or liquid at the time of ingestion. Wait for at least 30 minutes to eat or drink after taking EOHILIA.
- Administer EOHILIA as follows:
  1. Do NOT mix EOHILIA with food or liquid.
  2. Shake the EOHILIA packet for at least 10 seconds prior to opening.
  3. Squeeze the packet from the bottom to the top directly into the mouth. Repeat 2 to 3 times until the EOHILIA packet is empty.
  4. Swallow all the EOHILIA suspension.
  5. Do not eat or drink for 30 minutes after taking EOHILIA. After 30 minutes, rinse mouth with water and spit out the contents without swallowing [see Warnings and Precautions (5.2)].
- Avoid consumption of grapefruit juice for the duration of therapy with EOHILIA [see Drug Interactions (7.1)].

3 DOSAGE FORMS AND STRENGTHS

Oral suspension: 2 mg/10 mL unit-dose packets of a white to yellow viscous suspension with cherry flavoring.

4 CONTRAINDICATIONS

EOHILIA is contraindicated in patients with hypersensitivity to budesonide. Serious hypersensitivity reactions, including anaphylaxis, have occurred with oral budesonide products [see Adverse Reactions (6.2)].

5 WARNINGS AND PRECAUTIONS

5.1 Hypercorticism and Adrenal Axis Suppression

Systemic effects such as hypercorticism and adrenal axis suppression may occur with use of corticosteroids, including EOHILIA. Monitor patients for signs and symptoms of hypercorticism and adrenal axis suppression and consider reducing the dosage of EOHILIA [see Adverse Reactions (6.1), Clinical Pharmacology (12.2)].

Patients with moderate to severe hepatic impairment (Child-Pugh Class B and C, respectively) could be at an increased risk of hypercorticism and adrenal axis suppression due to an increased systemic exposure of oral budesonide. Use is not recommended in patients with severe hepatic impairment (Child-Pugh Class C) and monitoring for signs and/or symptoms of hypercorticism is recommended in patients with moderate hepatic impairment (Child-Pugh Class B) [see Use in Specific Populations (8.6), Clinical Pharmacology (12.3)].

Corticosteroids, including EOHILIA, can reduce the response of the hypothalamus-pituitary-adrenal (HPA) axis to stress. In situations where patients are subject to trauma, surgery, infection, or other stress situations, supplementation with a systemic corticosteroid is recommended.

5.2 Immunosuppression and Increased Risk of Infection

Corticosteroids, including EOHILIA, suppress the immune system and increase the risk of infection with any pathogen, including viral, bacterial, fungal, protozoan, or helminthic pathogens. Corticosteroids can:

- Reduce resistance to new infections
- Exacerbate existing infections
- Increase the risk of disseminated infections
- Increase the risk of reactivation or exacerbation of latent infections
- Mask some signs of infection

Corticosteroid-associated infections can be mild but can be severe and at times fatal. The rate of infectious complications increases with increasing corticosteroid dosages.

Monitor patients for the development of infection and consider discontinuation of EOHILIA if the patient develops an infection while on treatment.

Tuberculosis

If corticosteroids are used in patients with latent tuberculosis or tuberculin reactivity, reactivation of tuberculosis may occur. Closely monitor such patients for reactivation while receiving EOHILIA.

Varicella Zoster and Measles Viral Infections

Varicella and measles can have a serious or even fatal course in non-immune pediatric and adult patients taking corticosteroids. In corticosteroid-treated patients who have not had these diseases or are non-immune, particular care should be taken to avoid exposure to varicella and measles:

- If an EOHILIA-treated patient is exposed to varicella, prophylaxis with varicella zoster immune globulin may be indicated. If varicella develops, treatment with antiviral agents may be considered.
- If an EOHILIA-treated patient is exposed to measles, prophylaxis with immunoglobulin may be indicated.

Hepatitis B Virus Reactivation

Hepatitis B virus reactivation can occur in patients who are hepatitis B carriers treated with immunosuppressive dosages of corticosteroids. Reactivation can also occur infrequently in corticosteroid-treated patients who appear to have resolved hepatitis B infection.

Prior to starting treatment with EOHILIA, for patients who show evidence of hepatitis B infection, recommend consultation with physicians with expertise in managing hepatitis B regarding monitoring and consideration for hepatitis B antiviral therapy.

Fungal Infections

Corticosteroids may exacerbate systemic fungal infections; therefore, avoid EOHILIA use in the presence of such infections.

Amebiasis

Corticosteroids may activate latent amebiasis. Therefore, it is recommended that latent amebiasis or active amebiasis be ruled out before initiating EOHILIA in patients who have spent time in the tropics or patients with unexplained diarrhea.

Strongyloides Infestation

Avoid EOHILIA in patients with known or suspected Strongyloides (threadworm) infection. Corticosteroid-induced immunosuppression may lead to Strongyloides superinfection and dissemination with widespread larval migration, often accompanied by severe enterocolitis and potentially fatal gram-negative septicemia.

Cerebral Malaria

Avoid corticosteroids, including EOHILIA, in patients with cerebral malaria.

Ocular Herpes Simplex

Avoid corticosteroids, including EOHILIA, in patients with active ocular herpes simplex.

Localized Infections

In clinical trials with EOHILIA, localized infections with Candida albicans occurred in the mouth, throat, and esophagus in some subjects [see Adverse Reactions (6.1)]. Do not eat or drink for 30 minutes after taking EOHILIA. After 30 minutes, rinse mouth with water and spit without swallowing [see Dosage and Administration (2.2)]. If oropharyngeal or esophageal candidiasis develops, treat with appropriate local or systemic antifungal therapy and consider discontinuing treatment with EOHILIA.

5.3 Erosive Esophagitis

Erosive esophagitis occurred in subjects who received EOHILIA in a 12-week clinical trial. None of the subjects had erosions at baseline esophagogastroduodenoscopy (EGD), and most were receiving concomitant therapy with a proton pump inhibitor (PPI) during the trial [see Adverse Reactions (6.1)].

Advise patients or caregivers to report new onset or worsening signs or symptoms of erosive esophagitis to their healthcare provider. Consider endoscopic evaluation as appropriate.

5.4 Effect on Growth

Use of corticosteroids may cause a reduction of growth velocity in pediatric patients. Monitor the growth of pediatric patients on EOHILIA. The maximum recommended duration of treatment with EOHILIA is 12 weeks [see Dosage and Administration (2.1)].

5.5 Symptoms of Steroid Withdrawal in Patients Transferred from Other Systemic Corticosteroids

Monitor patients who are transferred from corticosteroid treatment with high systemic effects to corticosteroids with lower systemic availability, such as EOHILIA, since symptoms attributed to withdrawal of steroid therapy, including those of acute adrenal axis suppression or benign intracranial hypertension, may develop. Adrenocortical function monitoring may be required in these patients and the dose of corticosteroid treatment with high systemic effects should be reduced cautiously.

Replacement of systemic corticosteroids with EOHILIA may unmask allergies (e.g., rhinitis and eczema), which were previously controlled by the systemic drug.

5.6 Other Corticosteroid Effects

Monitor patients with hypertension, diabetes mellitus, osteoporosis, peptic ulcer, glaucoma or cataracts, or with a family history of diabetes or glaucoma, or with any other condition where corticosteroids may have unwanted effects.

5.7 Kaposi’s Sarcoma

Kaposi’s sarcoma has been reported to occur in patients receiving corticosteroid therapy, most often for chronic conditions. Discontinuation of corticosteroids may result in clinical improvement of Kaposi’s sarcoma. The maximum recommended duration of treatment with EOHILIA is 12 weeks [see Dosage and Administration (2.1)].

6 ADVERSE REACTIONS

The following serious adverse reactions are described in greater detail in other sections of the labeling:

- Hypercorticism and adrenal axis suppression [see Warnings and Precautions (5.1)]
- Immunosuppression and increased risk of infections [see Warnings and Precautions (5.2)]
- Erosive esophagitis [see Warnings and Precautions (5.3)]
- Effect on growth [see Warnings and Precautions (5.4)]
- Symptoms of steroid withdrawal in those patients transferred from other systemic corticosteroids [see Warnings and Precautions (5.5)]
- Other corticosteroid effects [see Warnings and Precautions (5.6)]
- Kaposi’s sarcoma [see Warnings and Precautions (5.7)]

6.1 Clinical Trials Experience

Because clinical trials are conducted under widely varying conditions, adverse reaction rates observed in the clinical trials of a drug cannot be directly compared to rates in the clinical trials of another drug and may not reflect the rates observed in practice.

The safety of EOHILIA in 410 adults and pediatric subjects 11 years of age and older with EoE was evaluated in two 12-week, double-blind, placebo-controlled studies (Study 1 and Study 2). In these studies, 263 subjects received EOHILIA [see Clinical Studies (14)].

Common Adverse Reactions

The most common adverse reactions reported in Study 1 are shown in Table 1.

Table 1: Common Adverse Reactions [reported in at least 2% of subjects in the EOHILIA group and at a rate greater than placebo.] in Adult and Pediatric Subjects 11 Years of Age and Older with EoE in Study 1
ADVERSE REACTIONS | EOHILIA 2 mg Twice Daily N = 213 | Placebo N = 105
Respiratory tract infection [includes acute sinusitis, sinusitis, nasopharyngitis, respiratory tract infection, respiratory tract infection viral, upper respiratory tract infection, viral upper respiratory tract infection, rhinitis] | 13% | 11%
Gastrointestinal mucosal candidiasis [includes esophageal candidiasis, oropharyngeal candidiasis, oral candidiasis] | 8% | 2%
Headache [includes headache, migraine] | 5% | 2%
Gastroenteritis | 3% | 1%
Throat irritation [includes throat irritation, oropharyngeal pain] | 3% | 2%
Adrenal suppression [includes adrenal suppression, adrenal insufficiency] | 2% | 0
Erosive esophagitis [includes esophagitis only where erosions were present at the esophagogastroduodenoscopy conducted after 12 weeks of treatment] | 2% | 0

Specific Adverse Reactions

Erosive Esophagitis

Erosive esophagitis occurred in 4/213 (2%) of EOHILIA-treated subjects in Study 1. These subjects had no erosions present at the baseline esophagogastroduodenoscopy (EGD). At EGD after 12 weeks of treatment with EOHILIA, 2 subjects had Los Angeles (LA) classification grade A, 1 subject had LA grade B, and 1 subject had LA grade C erosive esophagitis. All but one of the four subjects developed erosive esophagitis while receiving concomitant therapy with a PPI. No cases of erosive esophagitis were reported in Study 2 [see Warnings and Precautions (5.3)].

Less Common Adverse Reactions

Adverse reactions reported in less than 2% of subjects treated with EOHILIA and at a greater rate than placebo in Study 1 are listed below:

Cardiac disorders: Palpitations

Gastrointestinal disorders: Dry mouth, dyspepsia, erosive duodenitis, gastrointestinal motility disorder, esophageal food impaction, palatal swelling

General disorders and administration site conditions: Fatigue, feeling abnormal

Infections and infestations: Fungal skin infection, paronychia, pneumonia, sepsis, bronchitis

Investigations: Transaminases increased, hyperkalemia

Metabolism and nutrition disorders: Dyslipidemia

Musculoskeletal and connective tissue disorders: Arthralgia, muscle spasms

Nervous system disorders: Dysgeusia, syncope, tremor

Psychiatric disorders: Depression, irritability, restlessness

Respiratory, thoracic, and mediastinal disorders: Nasal congestion

Skin and subcutaneous tissue disorders: Hirsutism, dermatitis acneiform

Vascular disorders: Hypertension

The safety profile of EOHILIA in Study 2 was generally similar to Study 1.

6.2 Postmarketing Experience

The following adverse reactions have been reported during post-approval use of oral budesonide products. Because these reactions are reported voluntarily from a population of uncertain size, it is not always possible to reliably estimate their frequency or establish a causal relationship to drug exposure.

Hypersensitivity Reactions: Anaphylaxis

Nervous System Disorders: Benign intracranial hypertension

Psychiatric Disorders: Mood swings

7 DRUG INTERACTIONS

7.1 CYP3A4 Inhibitors

Budesonide is a substrate for CYP3A4. Concomitant use of budesonide with CYP3A4 inhibitors (e.g., ketoconazole, itraconazole, ritonavir, indinavir, saquinavir, erythromycin, cyclosporine, grapefruit juice) can increase systemic budesonide concentrations [see Clinical Pharmacology (12.3)]. Avoid concomitant use of CYP3A4 inhibitors, including grapefruit juice, with EOHILIA [see Dosage and Administration (2.2)].

8 USE IN SPECIFIC POPULATIONS

8.1 Pregnancy

Risk Summary

The available data from published case series, epidemiological studies, and reviews with oral budesonide use in pregnant women have not identified a drug-associated risk of major birth defects, miscarriage, or other adverse maternal outcomes. Infants exposed to in-utero corticosteroids, including EOHILIA, are at risk for hypoadrenalism (see Clinical Considerations). In animal reproduction studies, subcutaneous administration of budesonide during organogenesis in pregnant rats (at doses up to approximately 1.2 times the maximum recommended human dose, based on body surface area [BSA]) or pregnant rabbits (at doses approximately 0.14 times the maximum recommended human dose, based on body surface area [BSA]) resulted in increased fetal loss, decreased pup weights, and skeletal abnormalities. Maternal toxicity was observed in both rats and rabbits at these dose levels (see Data). Based on animal data, advise pregnant women of the potential risk to a fetus.

The background risk of major birth defects and miscarriage in the indicated population is unknown. All pregnancies have a background risk of birth defect, loss, or other adverse outcomes. In the U.S. general population, the estimated background risk of major birth defects and miscarriage in clinically recognized pregnancies is 2% to 4% and 15% to 20%, respectively.

Clinical Considerations

Fetal/Neonatal Adverse Reactions

Hypoadrenalism may occur in infants born of mothers receiving corticosteroids during pregnancy. Infants should be carefully observed for signs of hypoadrenalism, such as poor feeding, irritability, weakness, and vomiting, and managed accordingly [see Warnings and Precautions (5.1)].

Data

Animal Data

Budesonide was teratogenic and embryolethal in rabbits and rats.

In an embryo-fetal development study in pregnant rats dosed subcutaneously with budesonide during the period of organogenesis from gestation days 6-15, there were effects on fetal development and survival at subcutaneous doses up to approximately 500 mcg/kg/day in rats (approximately 1.2 times the maximum recommended human dose [MRHD], based on body surface area [BSA]). In an embryo-fetal development study in pregnant rabbits dosed during the period of organogenesis from gestation days 6-18, there was an increase in maternal abortion, and effects on fetal development and reduction in litter weights at subcutaneous doses up to approximately 25 mcg/kg/day (approximately 0.14 times the MRHD, based on BSA). Maternal toxicity, including reduction in body weight gain, was observed at subcutaneous doses of 5 mcg/kg in rabbits (approximately 0.03 times the MRHD, based on BSA) and 500 mcg/kg in rats (approximately 1.2 times the MRHD, based on BSA).

In a peri- and post-natal development study, rats dosed subcutaneously with budesonide during the period of Day 15 post coitum to Day 21 postpartum, budesonide had no effects on delivery but did have an effect on growth and development of offspring. In addition, offspring survival was reduced and surviving offspring had decreased mean body weights at birth and during lactation at exposures 0.05 times the MRHD (on a mg/m^2 basis at maternal subcutaneous doses of 20 mcg/kg/day and higher). These findings occurred in the presence of maternal toxicity.

8.2 Lactation

Risk Summary

Lactation studies have not been conducted with oral budesonide, including EOHILIA, and no information is available on the effects of the drug on the breastfed infant or the effects of the drug on milk production. One published study reported that budesonide is present in human milk following maternal inhalation of budesonide (see Data). The developmental and health benefits of breastfeeding should be considered along with the mother’s clinical need for EOHILIA and any potential adverse effects on the breastfed infant from EOHILIA, or from the underlying maternal condition.

Data

One published study reported that budesonide is present in human milk following maternal inhalation of budesonide which resulted in infant doses approximately 0.3% to 1% of the maternal weight-adjusted dosage and a milk/plasma ratio ranging between 0.4 and 0.5. Budesonide plasma concentrations were not detected, and no adverse events were noted in the breastfed infants following maternal use of inhaled budesonide. The recommended daily dose of EOHILIA is higher (4 mg daily) compared with inhaled budesonide (up to 800 mcg daily) given to mothers in the above-described study.

The maximum budesonide plasma concentration following a 2 mg single dose and twice a day repeat dose of oral budesonide is approximately 0.92 ng/mL to 1.1 ng/mL which is up to 2.5 times higher than the 0.43 to 0.86 ng/mL for an 800 mcg daily dose of inhaled budesonide at steady state in the above inhalation study.

Assuming the coefficient of extrapolation between the inhaled and oral doses is constant across all dose levels, at therapeutic doses of EOHILIA, budesonide exposure to the nursing child may be up to 2.5 times higher than that by budesonide inhalation.

8.4 Pediatric Use

The safety and effectiveness of EOHILIA for 12 weeks of treatment for EoE have been established in pediatric patients 11 years of age and older. Use of EOHILIA for this indication is supported by adequate and well controlled studies in adults and pediatric subjects 11 years of age and older (Studies 1 and 2) with pharmacokinetic data in pediatric subjects aged 11 to 17 years of age. In Studies 1 and 2, the safety of EOHILIA in pediatric subjects 11 to 17 years of age was similar to the safety profile in adults [see Adverse Reactions (6.1), Clinical Pharmacology (12.3), and Clinical Studies (14)].

Systemic effects such as hypercorticism and adrenal axis suppression may occur with use of corticosteroids, including EOHILIA [see Warnings and Precautions (5.1), Adverse Reactions (6.1), and Clinical Pharmacology (12.2)].

Use of corticosteroids may cause a reduction of growth velocity in pediatric patients. Monitor the growth of pediatric patients on EOHILIA. The recommended duration of treatment with EOHILIA is 12 weeks [see Dosage and Administration (2.1)].

The safety and effectiveness of EOHILIA in pediatric patients less than 11 years of age have not been established.

Juvenile Animal Toxicity Data

In a juvenile rat study, budesonide was administered orally at doses of 0.05, 0.2, 0.6, and 1.5 mg/kg/day starting on postnatal day (PND) 22 for 91 consecutive days. All of the effects noted were associated with the pharmacology of the drug and manifested in a dose related manner, typical of corticosteroids. These included decreased body weight gain, adrenal atrophy, and effects on bone (decreased cellularity and bone length) and lymphoid tissues (decreased cellularity). The no observed adverse effect level (NOAEL) in juvenile rats was determined to be the 0.05 mg/kg/day. Plasma exposure (AUC) in rats at the NOAEL (0.05 mg/kg/day) was lower (approximately 0.8 times) than that in pediatric subjects (11 years to 17 years of age) at the MRHD.

In a juvenile toxicity study in dogs, budesonide was orally administered at doses of 0.05, 0.2, and 0.6 mg/kg/day (starting at approximately 7 weeks of age) for 91 consecutive days. The observations were dose-related and consistent with corticosteroid treatment. The effects included decreased body weight gain, distended abdomen and swelling associated with inguinal hernias, lymphocytic and leukocytic changes, adrenal atrophy, depletion in lymphoid organs (lymph nodes, spleen, thymus), and effects on skeletal development (decreased cellularity in bone marrow, bone growth, and skeletal muscle atrophy). The incidence and severity of the majority of the pharmacologically mediated effects decreased or resolved completely following the recovery period. A NOAEL could not be defined in juvenile dogs. Plasma exposure (AUC) at the lowest dose tested (0.05 mg/kg/day) was lower (approximately 0.4 times) than that in pediatric subjects (11 years to 17 years of age) at the MRHD.

8.5 Geriatric Use

Clinical studies of EOHILIA did not include sufficient numbers of subjects 65 years of age and older to determine whether they respond differently from younger adult subjects. In general, EOHILIA should be used with caution due to the potential for decreased hepatic function [see Warnings and Precautions (5.1)].

8.6 Hepatic Impairment

Patients with moderate to severe hepatic impairment (Child-Pugh Class B or Class C, respectively) could be at an increased risk of hypercorticism and adrenal axis suppression due to an increased systemic exposure to budesonide. Use is not recommended in patients with severe hepatic impairment (Child-Pugh Class C). The recommended dosage in patients with mild or moderate hepatic impairment (Child-Pugh Class A or Class B) is the same as the recommended dosage in patients with normal hepatic function. In patients with moderate hepatic impairment (Child-Pugh Class B), monitor for signs and/or symptoms of hypercorticism [see Warnings and Precautions (5.1), Clinical Pharmacology (12.3)].

10 OVERDOSAGE

Treatment of acute overdosage consists of immediate gastric lavage or emesis followed by supportive and symptomatic therapy.

Use of corticosteroids, such as EOHILIA, at excessive doses or for prolonged periods, increases the risk of systemic corticosteroid effects such as hypercorticism and adrenal axis suppression [see Warnings and Precautions (5.1)].

11 DESCRIPTION

EOHILIA (budesonide oral suspension) contains budesonide, a synthetic corticosteroid.

Budesonide is designated chemically as (RS)-11β, 16α, 17,21-tetrahydroxypregna-1,4-diene-3,20-dione cyclic 16,17-acetal with butyraldehyde. Budesonide is a mixture of two epimers (22R and 22S). The empirical formula of budesonide is C25H34O6 and its molecular weight is 430.53. Its structural formula is:

Budesonide is a white or almost-white, crystalline powder that is freely soluble in chloroform, sparingly soluble in alcohol and practically insoluble in water and heptane.

EOHILIA (budesonide oral suspension) is a white to yellow, thixotropic, viscous suspension. Each 10 mL of EOHILIA contains 2 mg of budesonide. The oral suspension contains the following inactive ingredients: acesulfame potassium, ascorbic acid, Avicel® RC-591, cherry flavor, citric acid, dextrose, disodium ethylenediaminetetraacetic acid (EDTA), glycerin, Magnasweet® 110, maltodextrin, polysorbate 80, potassium sorbate, sodium ascorbate, sodium benzoate, sodium citrate, and purified water. Excipients contain no ingredient made from a gluten-containing grain (wheat, barley, or rye).

12 CLINICAL PHARMACOLOGY

12.1 Mechanism of Action

Budesonide is an anti-inflammatory corticosteroid and has a high glucocorticoid effect and a weak mineralocorticoid effect, and the affinity of budesonide to glucocorticoid receptors, which reflects the intrinsic potency of the drug, is about 200-fold that of cortisol and 15-fold that of prednisolone.

The precise mechanism of corticosteroid actions on inflammation in EoE is not known. Inflammation is an important component in the pathogenesis of EoE. Corticosteroids have a wide range of inhibitory activities against multiple cell types (e.g., mast cells, eosinophils, neutrophils, macrophages, and lymphocytes) and mediators (e.g., histamine, eicosanoids, leukocytes and cytokines) involved in allergic inflammation.

12.2 Pharmacodynamics

In Study 1, blood samples to detect cortisol levels (stimulated and unstimulated) were collected in the morning for all subjects [see Clinical Studies (14)]. At baseline, 4% of EOHILIA-treated subjects and 5% of placebo-treated subjects had abnormal peak adrenocorticotropic hormone (ACTH)-stimulated serum cortisol values, with abnormal defined as ≤18 mcg/dL. After 12 weeks of treatment, 9% of EOHILIA-treated subjects and 3% of placebo-treated subjects had abnormal peak ACTH-stimulated serum cortisol values [see Warnings and Precautions (5.1), Adverse Reactions (6.1)].

12.3 Pharmacokinetics

Budesonide geometric mean (%CV) maximum plasma concentration (Cmax) was 915 (59) pg/mL and area under the time concentration curve at 12 hours (AUC0-12h) was 5071 (58) pg•h/mL after repeated oral administration of EOHILIA 2 mg twice daily in adult subjects with EoE. Based on population pharmacokinetic analysis, there was no difference in pharmacokinetics between healthy adults and adult subjects with EoE.

Absorption

The median (range) time to reach budesonide peak plasma concentration (tmax) was 2 hours (range 0.5 to 4 hours) after oral administration of EOHILIA 2 mg twice daily in adult subjects with EoE. Following repeated (twice daily) oral administration of EOHILIA, the systemic exposure of budesonide was increased dose proportionally in the dose range of 0.5 to 2 mg (0.25 times the recommended dose and up to the recommended dose).

The oral bioavailability of budesonide in healthy subjects is estimated to be 14% under fasting state.

Effect of Food

A high-fat, high-calorie meal (800-1000 calories and approximately 50% fat) administered to healthy subjects increased the AUC of budesonide by 26% and decreased the Cmax by 13% following a single dose of EOHILIA compared to fasting conditions. Median time to reach peak plasma concentration was delayed approximately 1 hour with the intake of a high-fat, high-calorie meal. The increase in systemic exposure of budesonide due to food effect is not expected to be clinically meaningful.

Distribution

The mean volume of distribution (Vss/F) of budesonide is 1886 L after repeated oral administration of EOHILIA. Plasma protein binding was estimated to be 85% to 90% in the concentration range 0.43 to 99.02 ng/mL. The erythrocyte/plasma partition ratio at clinically relevant concentrations was about 0.8.

Elimination

Budesonide has a high plasma clearance, 0.9 to 1.8 L/min approaching the estimated liver blood flow, suggesting that budesonide is a high hepatic clearance drug. The mean plasma elimination half-life (t1/2) of budesonide after administration of EOHILIA was 3.3 hours.

Metabolism

Following oral absorption, budesonide is subject to high first pass metabolism (80% to 90%). In vitro, budesonide is biotransformed, mainly by CYP3A4, to its 2 major metabolites, 6beta-hydroxy budesonide and 16alpha-hydroxy prednisolone. The corticosteroid activity of these metabolites was negligible (less than1/100) in relation to that of the parent compound.

Excretion

Budesonide is excreted in urine and feces in the form of metabolites. After oral as well as intravenous administration of micronized [^3H]-budesonide, approximately 60% of the recovered radioactivity was found in urine. The major metabolites, including 6beta-hydroxy budesonide and 16alpha-hydroxy prednisolone, are mainly renally excreted, intact or in conjugated forms. No unchanged budesonide was detected in urine.

Specific Populations

Pediatric Patients

The pharmacokinetics of budesonide were evaluated in pediatric subjects aged 11 years to 17 years (n=10) following oral administration of EOHILIA 2 mg twice a day. The median (range) time to peak plasma concentration of budesonide was 1 (0.5, 2) hour, the mean (%CV) Cmax was 946 (61%) pg/mL and the mean (%CV) AUC0-8h was 3849 (51%) pg•h/mL.

Based on a population pharmacokinetic analysis, the steady-state exposure following EOHILIA 2 mg twice daily is predicted to be comparable between pediatric subjects (11 to less than 18 years) and adults (18 years and older).

Patients with Hepatic Impairment

In subjects with mild (Child-Pugh Class A, n=4) or moderate (Child-Pugh Class B, n=4) hepatic impairment, budesonide 4 mg was administered orally as a single dose. The subjects with moderate hepatic impairment had a 3.5-fold higher AUC compared to the healthy subjects with normal hepatic function while the subjects with mild hepatic impairment had an approximately 1.4-fold higher AUC. The Cmax values demonstrated similar increases [see Warnings and Precautions (5.1)]. The increased systemic exposure in subjects with mild hepatic impairment was not considered to be clinically relevant. Subjects with severe hepatic impairment (Child-Pugh Class C) were not studied [see Use in Specific Populations (8.6)].

Drug Interaction Studies

Budesonide is a substrate of CYP3A4. Inhibitors of CYP3A4 can increase the plasma concentrations of budesonide several-fold. Conversely, induction of CYP3A4 potentially could result in the lowering of budesonide plasma concentrations [see Dosage and Administration (2.2) and Drug Interactions (7.1)].

Budesonide is a substrate of P-gp, but not a substrate of BCRP, OATP1B1, OATP1B3, OAT1, OAT3, or OCT2. The role of P-gp on budesonide disposition is anticipated to be minimal due to CYP3A-mediated clearance.

Effects of Other Drugs on Budesonide

Ketoconazole

In an open, non-randomized, cross-over study, 6 healthy subjects were given budesonide 10 mg as a single dose (5-times the recommended dose of EOHILIA), either alone or concomitantly with the last ketoconazole dose of 3 days treatment with ketoconazole 100 mg twice daily. Coadministration of ketoconazole resulted in an eight-fold increase in AUC of budesonide, compared to budesonide alone [see Drug Interactions (7.1)].

Grapefruit Juice

In an open, randomized, cross-over study, 8 healthy subjects were given budesonide delayed-release capsules 3 mg (1.5-times the recommended dose of EOHILIA), either alone, or concomitantly with 600 mL concentrated grapefruit juice (which inhibits CYP3A4 activity predominantly in the intestinal mucosa), on the last of 4 daily administrations. Concomitant administration of grapefruit juice resulted in a 2-fold increase of the bioavailability of budesonide compared to budesonide alone [see Drug Interactions (7.1)].

Oral Contraceptives (CYP3A4 Substrates)

In a parallel study, the pharmacokinetics of budesonide were not significantly different between healthy female subjects who received oral contraceptives containing desogestrel 0.15 mg and ethinyl estradiol 30 mcg and healthy female subjects who did not receive oral contraceptives. Budesonide 4.5 mg (2.3-times the recommended dose of EOHILIA) once daily for one week did not affect the plasma concentrations of ethinyl estradiol, a CYP3A4 substrate.

Omeprazole

In a study in 11 healthy subjects, performed in a double-blind, randomized, placebo-controlled manner, the effect of 5 to 6 days treatment with omeprazole 20 mg once daily on the pharmacokinetics of budesonide administered as budesonide delayed-release capsules 9 mg (4.5-times the recommended dose of EOHILIA) as a single dose was investigated. Omeprazole 20 mg once daily did not affect the absorption or pharmacokinetics of budesonide.

Cimetidine

In an open, non-randomized, cross-over study, the potential effect of cimetidine on the pharmacokinetics of budesonide was studied. Six healthy subjects received cimetidine 1 gram daily (200 mg with meals and 400 mg at night) for 2 separate 3-day periods. Budesonide 4 mg (2-times the recommended dose of EOHILIA) was administered either alone or on the last day of one of the cimetidine treatment periods. Co-administration of cimetidine resulted in a 52% and 31% increase in the budesonide peak plasma concentration and the AUC of budesonide, respectively.

Effect of Budesonide on Other Drugs

Budesonide is not an inhibitor of CYP1A2, CYP2B6, CYP2C8, CYP2C9, CYP2C19, and CYP2D6 in vitro. Budesonide is not an inducer of CYP3A4, CYP1A2, or CYP2B6 at clinically relevant concentrations.

In vitro, budesonide is not a significant inhibitor of P-gp, BCRP, OATP1B1, OATP1B3, OAT1, OAT3, or OCT2 at clinically relevant concentrations.

13 NONCLINICAL TOXICOLOGY

13.1 Carcinogenesis, Mutagenesis, Impairment of Fertility

Carcinogenicity

Carcinogenicity studies with budesonide were conducted in rats and mice. In a 2-year study in Sprague-Dawley rats, budesonide caused a statistically significant increase in the incidence of gliomas in male rats at an oral dose of 50 mcg/kg/day (approximately 0.1 times the maximum recommended human dose [MRHD], based on the body surface area [BSA]). In addition, there were increased incidences of primary hepatocellular tumors in male rats at 25 mcg/kg (approximately 0.06 times the MRHD, based on BSA) and above. No tumorigenicity was seen in female rats at oral doses up to 50 mcg/kg/day (approximately 0.1 times the MRHD, based on BSA).

In an additional 2-year study in male Sprague-Dawley rats, budesonide caused no gliomas at an oral dose of 50 mcg/kg/day (approximately 0.1 times the MRHD, based on BSA); however, it caused a statistically significant increase in the incidence of hepatocellular tumors at this same oral dose of 50 mcg/kg/day. The concurrent reference corticosteroids (prednisolone and triamcinolone acetonide) showed similar findings. In a 91-week study in mice, budesonide caused no treatment-related carcinogenicity at oral doses up to 200 mcg/kg/day (approximately 0.2 times the MRHD, based on BSA).

Mutagenesis

Budesonide showed no evidence of genotoxic potential in the Ames test, the mouse lymphoma cell forward gene mutation (TK+/-) test, the human lymphocyte chromosome aberration test, the Drosophila melanogaster sex-linked recessive lethality test, the rat hepatocyte UDS test or the mouse micronucleus test.

Impairment of Fertility

In rats, budesonide had no effect on fertility at subcutaneous doses up to 80 mcg/kg/day (approximately 0.1 times the MRHD, based on BSA). However, it caused a decrease in prenatal viability and viability in pups at birth and during lactation, along with a decrease in maternal body weight gain, at subcutaneous doses of 20 mcg/kg/day (approximately 0.04 times the MRHD, based on BSA) and above. No such effects were noted at 5 mcg/kg/day (approximately 0.01 times the MRHD on a body surface area basis).

14 CLINICAL STUDIES

The efficacy and safety of EOHILIA 2 mg twice daily were evaluated in two multicenter, randomized, double-blind, parallel-group, placebo-controlled 12-week studies (Study 1 [NCT02605837] and Study 2 [NCT01642212]). Eligible subjects in Study 1 and Study 2 had esophageal inflammation defined as ≥15 eosinophils/high-power field (hpf) from at least 2 levels of the esophagus at baseline following a treatment course of a proton pump inhibitor (PPI) either prior to or during screening and at least 4 days of dysphagia as measured by the Dysphagia Symptom Questionnaire (DSQ) over a 2-week period prior to randomization. Concomitant use of stable doses of inhaled or intranasal steroids (for conditions other than EoE), PPIs, H2-receptor antagonists, antacids, antihistamines or anti-leukotrienes, and maintenance immunotherapy was allowed. In Study 1, subjects were enrolled after maintaining a stable diet for at least 3 months prior to screening and were instructed to maintain a stable diet throughout the study. Subjects were excluded if they were on a full liquid or 6-food elimination diet. In Study 2, subjects were instructed to maintain a stable diet throughout the study. In Study 1 and Study 2, subjects were instructed to not eat or drink for 30 minutes after taking the drug and then to rinse their mouth with water and spit out the contents without swallowing prior to resuming normal oral intake.

A total of 318 subjects (277 adults and 41 pediatric subjects) were randomized and received at least one dose of study drug (EOHILIA or placebo) in Study 1. The mean age of the study population was 34 years (range 11 to 56 years). Sixty percent of subjects were male, 95% were White, and 3% were Hispanic or Latino. Over 80% of the subjects were on concomitant PPI. The mean (SD) DSQ combined scores at baseline were 30.3 (13.9) and 30.4 (13.1) in the EOHILIA and placebo groups, respectively.

A total of 92 subjects (58 adults and 34 pediatric subjects) were randomized and received at least one dose of study drug (EOHILIA or placebo) in Study 2. The mean age of the study population was 22 years (range 11 to 42 years). Sixty-eight percent of subjects were male, 95% were White, and 1% were Hispanic or Latino. Over 65% of the subjects were on concomitant PPI. The mean (SD) DSQ combined scores at baseline were 30.7 (16.0) and 29.0 (13.5) in the EOHILIA and placebo groups, respectively.

Study 1 and Study 2 evaluated efficacy endpoints of histologic remission (defined as a peak eosinophil count of ≤6/hpf across all available esophageal levels) and the absolute change from baseline in subject-reported DSQ combined score after 12 weeks of treatment.

Efficacy results for Study 1 and Study 2 are presented in Table 2.

Table 2: Efficacy Results of EOHILIA in Adult and Pediatric Subjects 11 Years of Age and Older with EoE after 12 Weeks (Study 1 and Study 2)
 | Study 1 |  |  | Study 2
 | EOHILIA 2 mg Twice Daily N=213 | Placebo N=105 | Treatment difference and 95% CI [For histological remission, the difference in percentages and 95% Newcombe confidence intervals are estimated using Mantel Haenszel weights, adjusting for age group and diet restriction. For absolute change in DSQ score, the LS mean changes, standard errors, and differences are estimated using an ANCOVA model with treatment group, age group, diet restriction, and baseline measurement as covariates.] | EOHILIA 2 mg Twice Daily N=50 | Placebo N=42 | Treatment difference and 95%CI
Efficacy Endpoints
Proportion of subjects achieving histological remission (peak esophageal intraepithelial eosinophil count ≤6 eos/hpf) | 53.1% | 1.0% | 52.4% (43.3, 59.1) | 38.0% | 2.4% | 35.8% (17.2, 50.0)
Absolute change from baseline in DSQ combined score (0-84 [Total biweekly DSQ scores range from 0 to 84, higher scores indicate greater frequency and severity of dysphagia]), LS mean (SE) | -10.2 (1.5) | -6.5 (1.8) | -3.7 (-6.8, -0.6) | -14.5 (1.8) | -5.9 (2.1) | -8.6 (-13.7, -3.5)

During the last 2 weeks of the 12-week treatment periods in Study 1 and Study 2, a greater proportion of subjects randomized to EOHILIA experienced no dysphagia or only experienced dysphagia that “got better or cleared up on its own” compared to placebo, as measured by the subject-reported DSQ.

Additional Study

After completing Study 1, 48 subjects from the EOHILIA 2 mg treatment arm entered a double-blind randomized withdrawal extension study. These subjects received EOHILIA 2 mg twice daily or placebo for up to an additional 36 weeks. Treatment with EOHILIA did not demonstrate a statistically significant difference compared to subjects re-randomized to placebo for prespecified efficacy endpoints based on eosinophil count and/or clinical symptoms measured by the DSQ at Week 36.

16 HOW SUPPLIED/STORAGE AND HANDLING

- EOHILIA (budesonide oral suspension) 2 mg/10 mL is a white to yellow viscous suspension with cherry flavoring supplied in child-resistant unit-dose packets.
- EOHILIA is supplied in a carton containing 60 unit-dose packets (NDC 64764-105-60).

Store refrigerated or at controlled room temperature at 2°C to 25°C (36°F to 77°F). Excursions up to 30°C (86°F) are acceptable. Do NOT freeze.

17 PATIENT COUNSELING INFORMATION

Advise the patient or caregiver to read the FDA-approved patient labeling (Patient Information and Instructions for Use).

Hypercorticism and Adrenal Axis Suppression

Advise the patient or caregiver that EOHILIA may cause hypercorticism and adrenal axis suppression and to report any signs or symptoms to their healthcare provider (e.g., acne, bruise easily, ankle swelling, thicker body hair and facial hair, pink or purple stretch marks, a fatty pad or hump between the shoulders, tiredness, weakness, nausea and vomiting, low blood pressure) [see Warnings and Precautions (5.1)].

Immunosuppression and Increased Risk of Infection

Advise patients or caregivers to inform their healthcare provider if they develop a new or worsening infection and to contact their healthcare provider immediately if they are exposed to varicella or measles [see Warnings and Precautions (5.2)].

Inform the patient or caregiver that localized infections with Candida albicans may occur in the mouth, throat, and esophagus. Instruct patients to rinse the mouth with water 30 minutes after administration of EOHILIA and to spit out the contents without swallowing. Advise the patient or caregiver to contact the healthcare provider if the patient experiences signs or symptoms of oropharyngeal or esophageal candidiasis [see Dosage and Administration (2.2), Warnings and Precautions (5.2)].

Erosive Esophagitis

Advise patients or caregivers to report new onset or worsening signs or symptoms of erosive esophagitis (e.g., heartburn, chest pain, trouble swallowing) to their healthcare provider [see Warnings and Precautions (5.3)].

Effect on Growth

Advise patients or caregivers that corticosteroids can affect growth in pediatric patients and to report concerns regarding growth while taking EOHILIA to the healthcare provider [see Warnings and Precautions (5.4)].

Symptoms of Steroid Withdrawal in Patients Transferred from Other Systemic Corticosteroids

If transferring to EOHILIA from corticosteroid treatment with high systemic effects, advise the patient or caregiver to follow a taper schedule for systemic corticosteroids, as instructed by the healthcare provider. Advise patients or caregivers that replacement of other systemic corticosteroids with EOHILIA may unmask allergies (e.g., rhinitis and eczema), which were previously controlled by the other drug [see Warnings and Precautions (5.5)].

Kaposi’s Sarcoma

Advise patients or caregivers that Kaposi’s sarcoma has been reported in patients receiving corticosteroids for chronic conditions and to inform their healthcare provider if they experience signs or symptoms of Kaposi’s sarcoma [see Warnings and Precautions (5.7)].

Pregnancy

Advise female patients that EOHILIA may cause fetal harm and to inform their healthcare provider with a known or suspected pregnancy [see Use in Specific Populations (8.1)].

Administration

Advise patients:

- Do NOT take EOHILIA with food or liquid at the time of ingestion. Wait for at least 30 minutes to eat or drink after taking EOHILIA [see Clinical Pharmacology (12.3)].
- Administer EOHILIA as follows:
  1. Do NOT mix EOHILIA with food or liquid.
  2. Shake EOHILIA packet for at least 10 seconds prior to opening.
  3. Squeeze the packet from the bottom to the top directly into the mouth. Repeat 2 to 3 times until the EOHILIA packet is empty.
  4. Swallow all the EOHILIA suspension.
  5. Do not eat or drink for 30 minutes after taking EOHILIA. After 30 minutes, rinse mouth with water and spit out the contents without swallowing [see Dosage and Administration (2.2), Warnings and Precautions (5.2)].
- Avoid consumption of grapefruit juice for the duration of EOHILIA therapy [see Drug Interactions (7.1)].

Distributed by:

Takeda Pharmaceuticals America, Inc.

Cambridge, MA 02142

EOHILIA and are trademarks of ViroPharma Biologics LLC.

TAKEDA and are registered trademarks of Takeda Pharmaceutical Company Limited.

©2025 Takeda Pharmaceuticals U.S.A., Inc. All rights reserved.

EOH357 R4

PATIENT INFORMATION
EOHILIA™ (ee-oh-HIL-ee-uh)
(budesonide oral suspension)

What is EOHILIA?
EOHILIA is a prescription oral corticosteroid medicine used for 12 weeks of treatment of Eosinophilic Esophagitis (EoE), in people 11 years and older.
EOHILIA has not been shown to be safe and effective for the treatment of EoE for longer than 12 weeks.
It is not known if EOHILIA is safe and effective in children younger than 11 years of age.

Who should not take EOHILIA?
Do not take EOHILIA if:

- you are allergic to budesonide.

Before you take EOHILIA tell your healthcare provider if you have any other medical conditions including if you:

- have liver problems.
- are planning to have surgery.
- have chicken pox or measles or have recently been near anyone with chicken pox or measles.
- have certain kinds of infection that have not been treated including:
  - fungal infections.
  - bacterial infections.
  - viral infections.
  - parasitic infections, including threadworm (Strongyloides) infections.
  - herpes simplex infection of the eye (ocular herpes simplex).
- have or had tuberculosis.
- have malaria of the brain (cerebral malaria).
- have an infection of the mouth, throat, or esophagus.
- have diabetes or glaucoma or have a family history of diabetes or glaucoma.
- have cataracts.
- have high blood pressure (hypertension).
- have low bone mineral density or osteoporosis.
- have stomach ulcers.
- are pregnant or plan to become pregnant. EOHILIA may harm your unborn baby. Talk to your healthcare provider about the possible risk to your unborn baby if you take EOHILIA when you are pregnant. Tell your healthcare provider right away if you become pregnant or think you may be pregnant during your treatment with EOHILIA.
- are breastfeeding or plan to breastfeed. It is not known if EOHILIA passes into your breast milk or if it will affect your baby. Talk to your healthcare provider about the best way to feed your baby if you take EOHILIA.

Tell your healthcare provider about all the medicines you take, including prescription and over-the counter medicines, vitamins, and herbal supplements. EOHILIA and other medicines may affect each other causing side effects.

How should I take EOHILIA?

- See the detailed Instructions for Use that comes with EOHILIA for information about how to prepare and take EOHILIA and how to properly store and throw away (dispose of) used EOHILIA packets.
- Take EOHILIA exactly as your healthcare provider tells you. Your healthcare provider will tell you how much EOHILIA to take.
- EOHILIA is taken by mouth, 2 times a day (1 time in the morning and 1 time in the evening).
- Do not mix EOHILIA with food or liquid.
- Do not eat or drink at the same time as taking EOHILIA. Wait to eat or drink at least 30 minutes after taking EOHILIA.
- Your healthcare provider may change your dose if needed. Do not change your dose or stop taking EOHILIA unless your healthcare provider tells you.

What should I avoid while taking EOHILIA?

- Avoid drinking grapefruit juice while taking EOHILIA. Drinking grapefruit juice can increase the level of EOHILIA in your blood.

What are the possible side effects of EOHILIA?
EOHILIA may cause serious side effects, including:

- Effects of having too much corticosteroid medicine in your blood (hypercorticism). Long-term use of EOHILIA may cause you to have elevated levels of corticosteroid medicine in your blood. Tell your healthcare provider if you have any of the following signs and symptoms:

- acne
- bruise easily
- rounding of your face
- ankle swelling

- thicker body hair and facial hair
- a fatty pad or hump between your shoulders (buffalo hump)
- pink or purple stretch marks on the skin of your abdomen, thighs, breasts and arms

- Adrenal suppression. Long-term use of EOHILIA can cause a condition in which the adrenal glands do not make enough steroid hormones (adrenal suppression). Tell your healthcare provider if you are under stress or if you have any of the following signs or symptoms:

- tiredness
- weakness

- nausea and vomiting
- low blood pressure

- Decreased ability of your body to fight infections (immunosuppression) and increased risk of infection. Corticosteroid medicines, including EOHILIA, lower the ability of your immune system to fight infections and increase the risk of infections caused by viruses, bacteria, fungi, protozoans, or certain parasites. Corticosteroid medicines, including EOHILIA can also:
  - make current infections worse
  - increase the risk of infections spreading (disseminated)
  - increase the risk of making infections active again or making infections worse that have not been active (latent)
  - hide (mask) some signs of infection

These infections can be mild but can be severe and lead to death. Your healthcare provider should check you closely for signs and symptoms of an infection while taking EOHILIA. Tell your healthcare provider right away about any signs or symptoms of a new or worsening infection while taking EOHILIA, including flu-like symptoms such as:

- fever
- chills
- stomach area (abdominal) pain
- aches
- diarrhea

- cough
- pain
- feeling tired
- nausea and vomiting

- Tuberculosis: If you have inactive (latent) tuberculosis, your tuberculosis may become active again while taking EOHILIA. Your healthcare provider should check you closely for signs and symptoms of tuberculosis while taking EOHILIA.
- Chicken pox and measles: People taking corticosteroid medicines, including EOHILIA, who have not had chicken pox or measles, should avoid contact with people who have these diseases. Tell your healthcare provider right away if you come in contact with anyone who has chicken pox or measles.
- Hepatitis B virus (HBV) reactivation: If you are a carrier of HBV, the virus can become an active infection again while taking EOHILIA. Your healthcare provider will test you for HBV before you start taking EOHILIA.
- Amebiasis: Inactive (latent) amebiasis may become an active infection while taking EOHILIA. Your healthcare provider should check you for amebiasis before you start taking EOHILIA if you have spent time in the tropics or have unexplained diarrhea.
- Fungal infections of the mouth (thrush), throat, and esophagus in patients using EOHILIA may occur. Symptoms of infection include white spots in the mouth, a burning or painful sensation in your mouth, redness inside of your mouth, difficulty with eating or swallowing, loss of taste, and cotton feeling in your mouth. Tell your healthcare provider if any of the above symptoms occur.

- Erosive esophagitis. EOHILIA can cause acid-related damage to the lining of the esophagus. Tell your healthcare provider if you notice any new or worsening signs or symptoms:

- heartburn

- chest pain

- trouble swallowing

- Effect on growth. Taking corticosteroids can affect your child’s growth. Tell your healthcare provider if you are worried about your child’s growth. Your healthcare provider may monitor the growth of your child while taking EOHILIA.

- Worsening of allergies. If you take certain other corticosteroid medicines to treat allergies, switching to EOHILIA may cause your allergies to come back. These allergies may include a skin condition called eczema or inflammation inside your nose (rhinitis). Tell your healthcare provider if any of your allergies become worse while taking EOHILIA.

- Kaposi’s sarcoma: Kaposi’s sarcoma has happened in people who receive corticosteroid therapy, most often for treatment of long-lasting (chronic) conditions.

The most common side effects of EOHILIA include:

- respiratory tract infection
- fungal infections of the mouth, throat and esophagus (thrush)
- headache
- infection of the stomach and intestine (gastroenteritis)

- sore throat
- adrenal suppression
- acid-related damage to the lining of the esophagus (erosive esophagitis)

Tell your healthcare provider if you have any side effect that bothers you or that does not go away.

These are not all the possible side effects of EOHILIA. For more information, ask your healthcare provider or pharmacist.

Call your doctor for medical advice about side effects. You may report side effects to FDA at 1-800-FDA-1088.

How should I store EOHILIA?
Store between 36°F to 77°F (2°C to 25°C). May be refrigerated. Do not freeze.
Keep EOHILIA and all medicines out of the reach of children.

General information about the safe and effective use of EOHILIA.
Medicines are sometimes prescribed for purposes other than those listed in a Patient Information leaflet. Do not use EOHILIA for a condition for which it was not prescribed.
Do not give EOHILIA to other people, even if they have the same symptoms that you have. It may harm them.
You can ask your pharmacist or healthcare provider for information about EOHILIA that is written for health professionals.

What are the ingredients in EOHILIA?
Active ingredient: budesonide
Inactive ingredients: acesulfame potassium, ascorbic acid, Avicel® RC‑591, cherry flavor, citric acid, dextrose, disodium ethylenediaminetetraacetic acid (EDTA), glycerin, Magnasweet® 110, maltodextrin, polysorbate 80, potassium sorbate, sodium ascorbate, sodium benzoate, sodium citrate, and purified water. Contains no ingredient made from a gluten-containing grain (wheat, barley, or rye).
Distributed by: Takeda Pharmaceuticals America, Inc., Cambridge, MA 02142
EOHILIA and are trademarks of ViroPharma Biologics LLC. TAKEDA and are registered trademarks of Takeda Pharmaceutical Company Limited.
©2025 Takeda Pharmaceuticals U.S.A., Inc. All rights reserved.
For more information, go to www.EOHILIA.com or call 1-877-TAKEDA-7 (1-877-825-3327).

This Patient Information has been approved by the U.S. Food and Drug Administration.

Revised: 1/2025

EOH357 R4

INSTRUCTIONS FOR USE
EOHILIA™ (ee-oh-HIL-ee-uh)
(budesonide oral suspension)

This Instructions for Use contains information on how to take EOHILIA.

Important Information You Need to Know Before Taking EOHILIA

For oral use only (take by mouth).

Take EOHILIA exactly as your healthcare provider tells you. Your healthcare provider will tell you how much EOHILIA to take.

- EOHILIA is taken by mouth, 2 times a day (1 time in the morning and 1 time in the evening).
- Do not mix EOHILIA with food or liquid.
- Avoid drinking grapefruit juice while taking EOHILIA.
- Do not eat or drink at the same time as taking EOHILIA. Wait to eat or drink at least 30 minutes after taking EOHILIA.
- Your healthcare provider may change your dose if needed. Do not change your dose or stop taking EOHILIA unless your healthcare provider tells you.

EOHILIA is provided as a unit-dose 10 mL packet intended for oral use.

Inspect package and do not take if:

- carton seal is broken or
- the packet is damaged or leaking.
- the expiration date (EXP) has passed.

Taking EOHILIA

How to take EOHILIA PACKET:

Step 1 | Figure A | - Do not take EOHILIA with food or liquid (see Figure A).
Step 2 | Figure B | - Shake the packet well for at least 10 seconds before opening (see Figure B). - Using scissors, cut along the dotted line straight across the top of the packet.
Step 3 | Figure C | - Take EOHILIA by squeezing the packet from the bottom to the top directly into the mouth (see Figure C). - Repeat 2 to 3 times until all the medicine is given. - Swallow all the EOHILIA suspension. - Throw away (discard) the empty packet in the household trash.
Step 4 | Figure D | - Do not eat or drink for 30 minutes after taking EOHILIA (see Figure D). - After 30 minutes, rinse your mouth with water and spit out the contents without swallowing.

Storing EOHILIA

Store between 36°F to 77°F (2°C to 25°C). May be refrigerated.

Do not freeze.

Keep EOHILIA and all medicines out of the reach of children.

Disposing of EOHILIA

Throw away (discard) the empty EOHILIA packet in the household trash.

For more information, go to www.EOHILIA.com or call 1-877-TAKEDA-7 (1-877-825-3327).

Distributed by:
Takeda Pharmaceuticals America, Inc.
Cambridge, MA 02142

EOHILIA and are trademarks of ViroPharma Biologics LLC.

TAKEDA and are registered trademarks of Takeda Pharmaceutical Company Limited.

©2025 Takeda Pharmaceuticals U.S.A., Inc. All rights reserved.

This Instructions for Use has been approved by the U.S. Food and Drug Administration.

Revised: 1/2025

EOH357 R4

PRINCIPAL DISPLAY PANEL - 10 mL packets Carton

NDC 64764-105-60
Rx Only

Eohilia™
(budesonide oral suspension)

2 mg/10 mL

For Oral Use

60
unit-dose
10 mL packets

Takeda